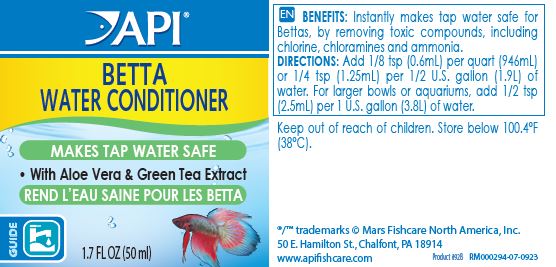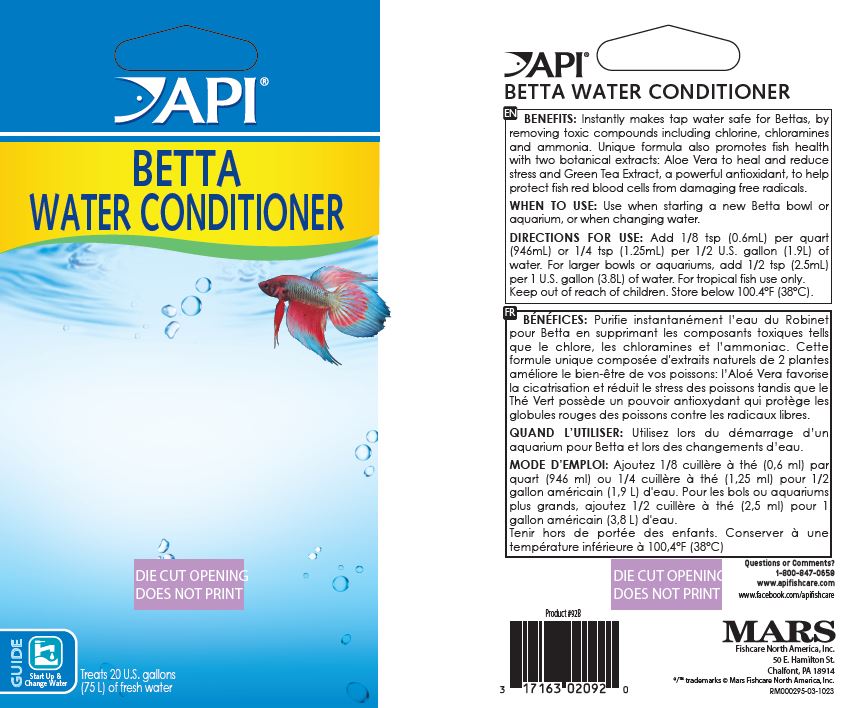 DRUG LABEL: API Betta Water Conditioner
NDC: 17163-092 | Form: LIQUID
Manufacturer: MARS FISHCARE NORTH AMERICA, INC
Category: animal | Type: OTC ANIMAL DRUG LABEL
Date: 20240410

ACTIVE INGREDIENTS: ALOE VERA LEAF 0.01 g/100 mL

Drug Facts

INDICATIONS AND USAGE

BENEFITS:

Instantly makes tap water safe for Bettas, by removing toxic compounds, including chlorine, chloramines and ammonia. Unique formula also promotes fish health with two botanical extracts: Aloe Vera to heal and reduce stress and Green Tea Extract, a powerful antioxidant. to help protect fish red blood cells from damaging free radicals.

WHEN TO USE:

Use when starting a new Betta bowl or aquarium, or when changing water.

DIRECTIONS:

Add 1/8 tsp (0.6mL) per quart (946mL) or 1/4 tsp (1.25 mL) per 1/2 U.S. gallon (1.9L) of water. For larger bowls or aquariums, add 1/2 tsp (2.5mL) per 1 U.S. gallon (3.8L) of water. For Tropical fish use only. Keep out of reach of children. Store below 100.4ºF (38ºC).

PACKAGE LABEL

API

BETTA

WATER CONDITIONER

MAKES TAP WATER SAFE

With Aloe Vera and Green Tea Extract

GUIDE

1.7 FL OZ (50ml)